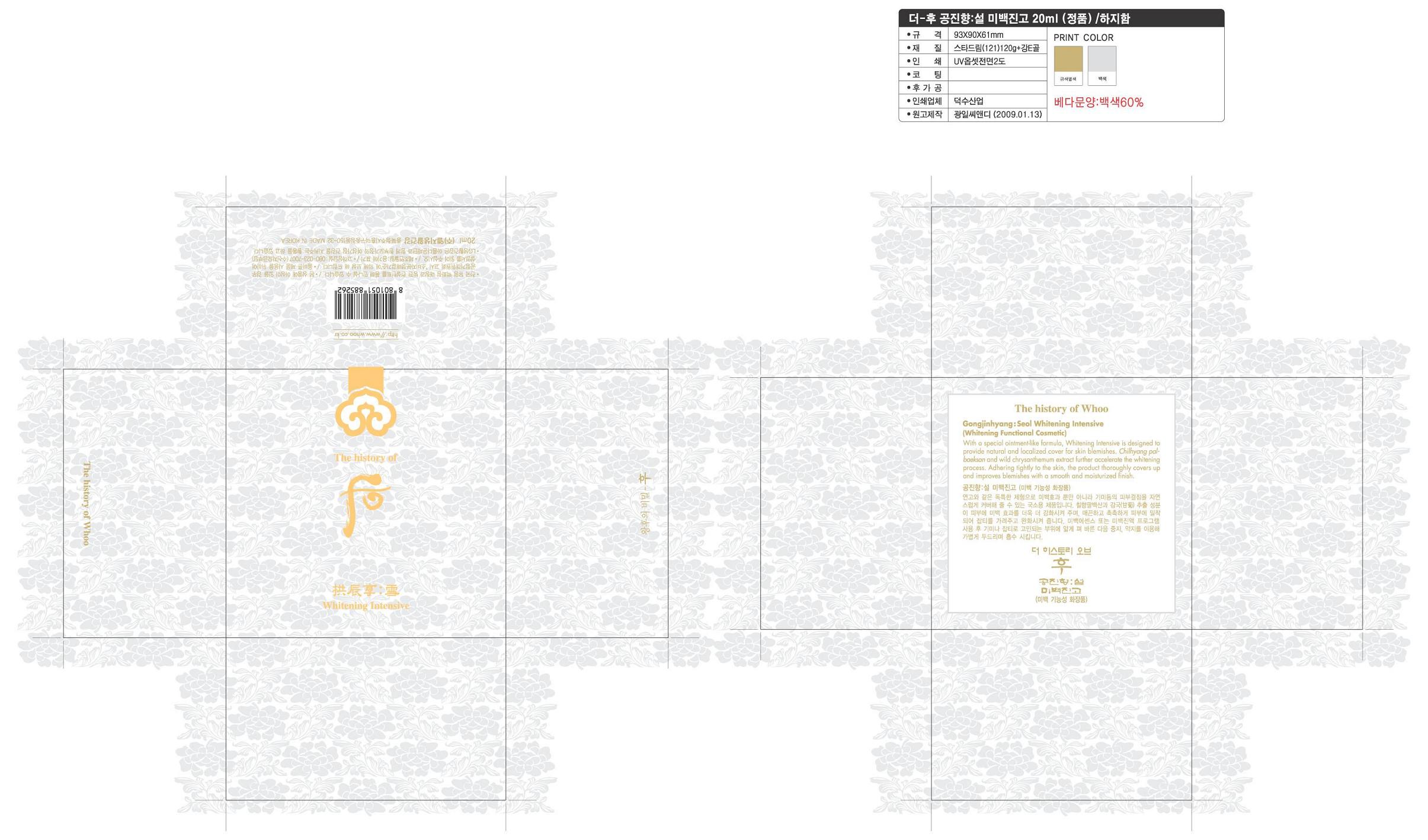 DRUG LABEL: Gongjinhyang Seol Whitening Intensive
NDC: 53208-374 | Form: CREAM
Manufacturer: LG Household and Healthcare, Inc.
Category: otc | Type: HUMAN OTC DRUG LABEL
Date: 20100503

ACTIVE INGREDIENTS: DIACETYL BENZOYL LATHYROL 0.1 mL/100 mL
INACTIVE INGREDIENTS: DIMETHICONE; SQUALANE; PARAFFIN; TALC; PROPYLPARABEN; FERROSOFERRIC OXIDE

Drug Facts

ACTIVE INGREDIENT

DIACETYL BENZOYL LATHYROL 0.1mL/100mL

WARNINGS AND PRECAUTIONS

For external use only

Keep out of reach of children. If swallowed, get medical help or contact a Poison Control Center right away.

WHEN USING

Keep out of eyes. Rinse with water to remove.

Stop use if a rash or irritation develops and lasts.

PACKAGE LABEL

The History of Whoo
Whitening Intensive